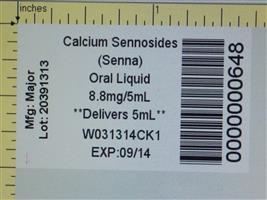 DRUG LABEL: Senna
NDC: 68151-0648 | Form: SYRUP
Manufacturer: Carilion Materials Management
Category: otc | Type: HUMAN OTC DRUG LABEL
Date: 20180206

ACTIVE INGREDIENTS: SENNOSIDES A AND B 8.8 mg/5 mL
INACTIVE INGREDIENTS: Methylparaben; propylene glycol; propylparaben; water; cocoa; sucrose

Senna Syrup

Drug Facts

*Senna Syrup is not manufactured or distributed by The Purdue Frederick Company, owners of the registered trademark Senokot®.

Active Ingredient (in each teaspoonful)

Sennosides 8.8 mg

Purpose

Laxative

Uses

relieves occasional constipation (irregularity), generally produces bowel movement in 6-12 hours

Warnings

Ask a doctor before use if you have

- stomach pain
- nausea
- vomiting
- Noticed a sudden change in bowel movements that continues over a period of 2 weeks

Do not use laxative products for longer than 1 week unless directed by a doctor

Ask a doctor or pharmacist before use if you are taking any other drug. Take this product two or more hours before or after other drugs. Laxatives may affect how other drugs work.

Stop use and ask a doctor if you have rectal bleeding or fail to have bowel movement after use of laxative. These may indicate a serious condition.

PREGNANCY OR BREAST FEEDING

If pregnant or breast-feeding, ask a professional before use.

Keep out of reach of children. In case of overdose, get medical help or contact a Poison Control Center right away.

Directions

Take preferably at bedtime or as directed by a doctor. Shake Well Before Using.

age | starting dose | maximum dosage
adults and children 12 years and older | 2 - 3 teaspoons once a day | 3 teaspoons twice a day
children 6 to under 12 years | 1 - 1 1/2 teaspoons once a day | 1 1/2 teaspoons twice a day
children 2 to under 6 years | 1/2 - 3/4 teaspoon once a day | 3/4 teaspoon twice a day
children under 2 years | ask a doctor | ask a doctor

Other information

- avoid excessive heat
- store at room temperature 15°- 30°C (59°- 86°F)

Inactive ingredients

cocoa distillate flavor, natural chocolate flavor, methylparaben, propylene glycol, propylparaben, purified water, sucrose

Questions?

To Report Adverse Drug Event Call (800) 616-2471

Distributed by: MAJOR® PHARMACEUTICALS
31778 Enterprise Drive
Livonia, MI 48150 USA

HOW SUPPLIED

Product: 68151-0648

NDC: 68151-0648-0 5 mL in a PACKAGE